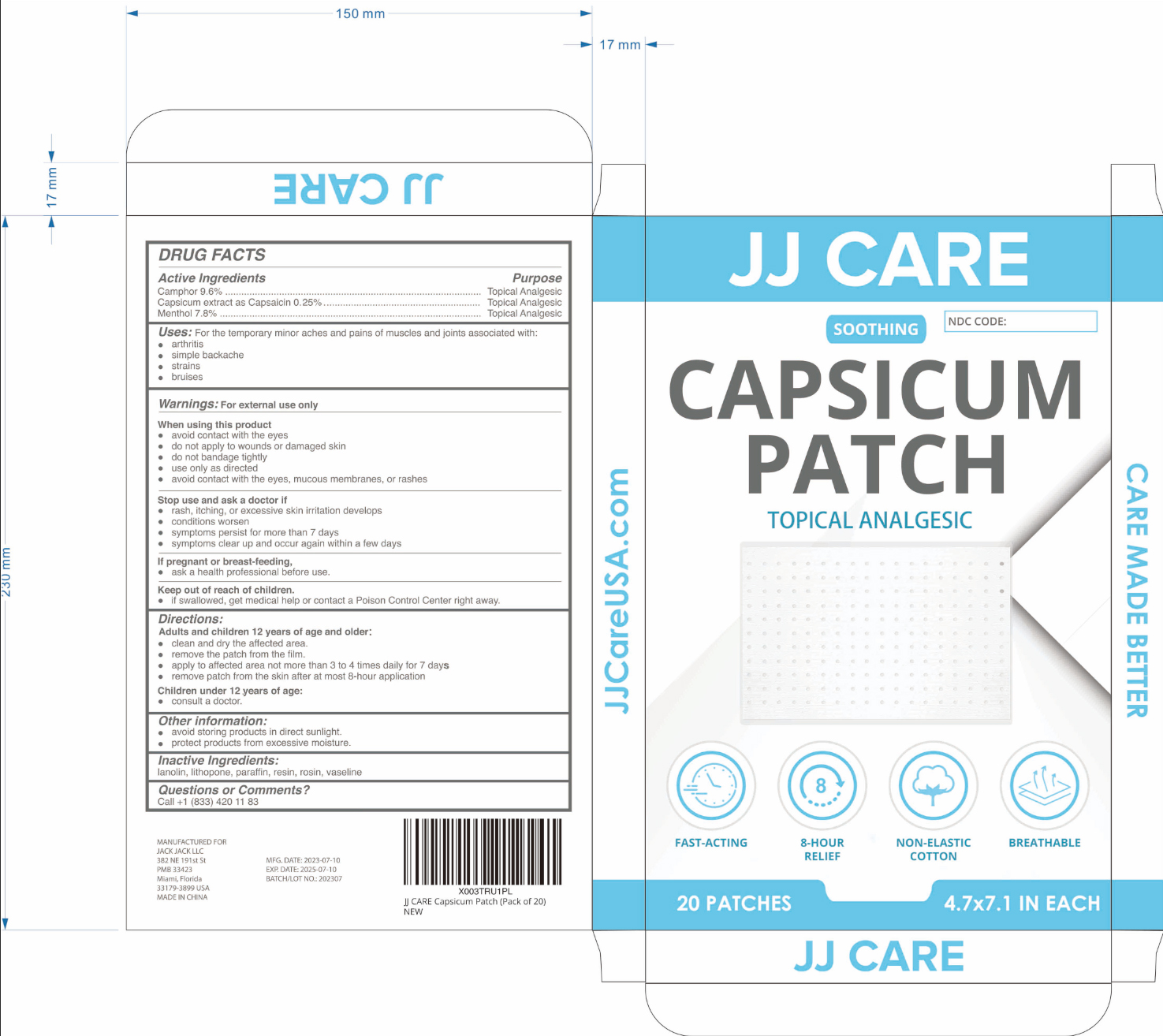 DRUG LABEL: Capsicum Patch
NDC: 81484-701 | Form: PATCH
Manufacturer: Anhui Miao De Tang Pharmaceutical Co., Ltd.
Category: otc | Type: HUMAN OTC DRUG LABEL
Date: 20231114

ACTIVE INGREDIENTS: MENTHOL 7.8 g/1 1; CAPSAICIN 0.25 g/1 1; CAMPHOR (SYNTHETIC) 9.6 g/1 1
INACTIVE INGREDIENTS: TERPENE RESIN; ROSIN; PETROLATUM; PARAFFIN; LANOLIN; LITHOPONE

Capsicum Patch

CAPSICUM PATCH

ACTIVE INGREDIENT

Camphor 9.6%

Capsicum extract as Capsaicin 0.25%

Menthol 7.8%

PURPOSE

For the temporary minor aches and pains of muscles and joints associated with:

· arthritis

· simple backache

· strains

· bruises

INDICATIONS AND USAGE

For the temporary minor aches and pains of muscles and joints associated with:

arthritis

simple backache

strains

bruises

TOPICAL ANALGESIC

WARNINGS

For external use only

When using this product

avoid contact with the eyes
do not apply to wounds or damaged skin
do not bandage tightly
use only as directed
avoid contact with the eyes, mucous membranes, or rashes

Stop use and ask a doctor if

rash, itching, or excessive skin irritation develops

conditions worsen
symptoms persist for more than 7 days

symptoms clear up and occur again within a few days

WHEN USING

lf pregnant or breast-feeding

ask a health professional before use.

Keep out of reach of children. if swallowed, get medical help or contact a Poison Control Center right away.

Stop use and ask a doctor if
rash, itching, or excessive skin irritation develops
conditions worsen
symptoms persist for more than 7 days

symptoms clear up and occur again within a few days

Keep out of reach of children.

STORAGE AND HANDLING

avoid storing products in direct sunlight.

protect products from excessive moisture.

INACTIVE INGREDIENT

lanolin, lithopone, paraffin, resin, rosin, vaseline

DOSAGE AND ADMINISTRATION

Adults and children 12 years of age and older:
clean and dry the affected area.

remove the patch from the film.

apply to affected area not more than 3 to 4 times daily for 7 days

remove patch from the skin after at most 8-hour application

Children under 12 years of age:

consult a doctor.